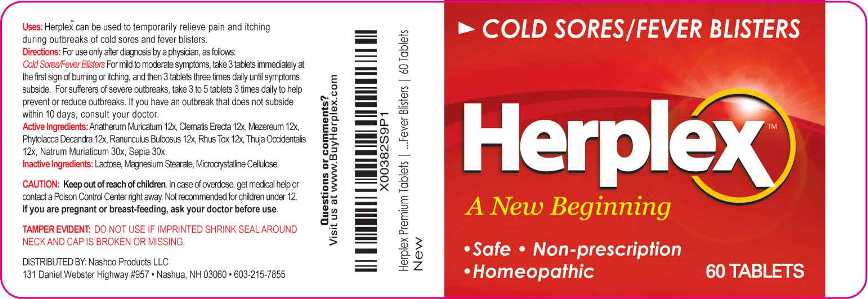 DRUG LABEL: Herplex
NDC: 72968-0003 | Form: TABLET
Manufacturer: Nashco Products LLC
Category: homeopathic | Type: HUMAN OTC DRUG LABEL
Date: 20240122

ACTIVE INGREDIENTS: CHRYSOPOGON ZIZANIOIDES ROOT 12 [hp_X]/1 1; CLEMATIS RECTA FLOWERING TOP 12 [hp_X]/1 1; DAPHNE MEZEREUM BARK 12 [hp_X]/1 1; PHYTOLACCA AMERICANA ROOT 12 [hp_X]/1 1; RANUNCULUS BULBOSUS WHOLE 12 [hp_X]/1 1; TOXICODENDRON PUBESCENS LEAF 12 [hp_X]/1 1; THUJA OCCIDENTALIS LEAFY TWIG 12 [hp_X]/1 1; SODIUM CHLORIDE 30 [hp_X]/1 1; SEPIA OFFICINALIS JUICE 30 [hp_X]/1 1
INACTIVE INGREDIENTS: LACTOSE MONOHYDRATE; MAGNESIUM PALMITOSTEARATE; CELLULOSE, MICROCRYSTALLINE

DRUG FACTS:

ACTIVE INGREDIENTS:

Anatherum Muricatum 12X, Clematis Erecta 12X, Mezereum 12X, Phytolacca Decandra 12X, Ranunculus Bulbosus 12X, Rhus Tox 12X, Thuja Occidentalis 12X, Natrum Muriaticum 30X, Sepia 30X.

USES:

Herplex can be used for temporarily relieve pain and itching during outbreads of cold sores and fever blisters.

WARNINGS:

CAUTION: Keep out of reach of children. In case of overdose, get medical help or contact a Poison Control Center right away. Not recommended for children under 12.

If you are pregnant or breast-feeding, ask your doctor before use.

TAMPER EVIDENT: DO NOT USE IF IMPRINTED SHRINK SEAL AROUND NECK AND CAP IS BROKEN OR MISSING.

Keep out of reach of children. In case of overdose, get medical help or contact a Poison Control Center right away.

DIRECTIONS:

For use only after diagnoses by a physician, as follows:

Cold Sores/Fever Blisters For mild to moderate symptoms, take 3 tablets immediately at the first sign of burning or itching, and then 3 tablets three times daily until symptoms subside For sufferers of severe outbreaks, take 3 to 5 tablets 3 times daily to help prevent or reduce outbreaks. If you have an outbreak that does not subside within 10 days, consult your doctor.

USES:

Herplex can be used for temporarily relieve pain and itching during outbreads of cold sores and fever blisters.

INACTIVE INGREDIENTS:

Lactose, Magnesium Stearate, Microcrystalline Cellulose.

QUESTIONS:

DISTRIBUTED BY: Nashco Products LLC

131 Daniel Webster Highway #957

Nashua, NH 03060

603-215-7855

Questions or comments?

Visit us at www.BuyHerplex.com

PACKAGE LABEL DISPLAY:

COLD SORES/FEVER BLISTERS

Herplex

A New Beginning

•Safe •Non-prescription

•Homeopathic

60 TABLETS